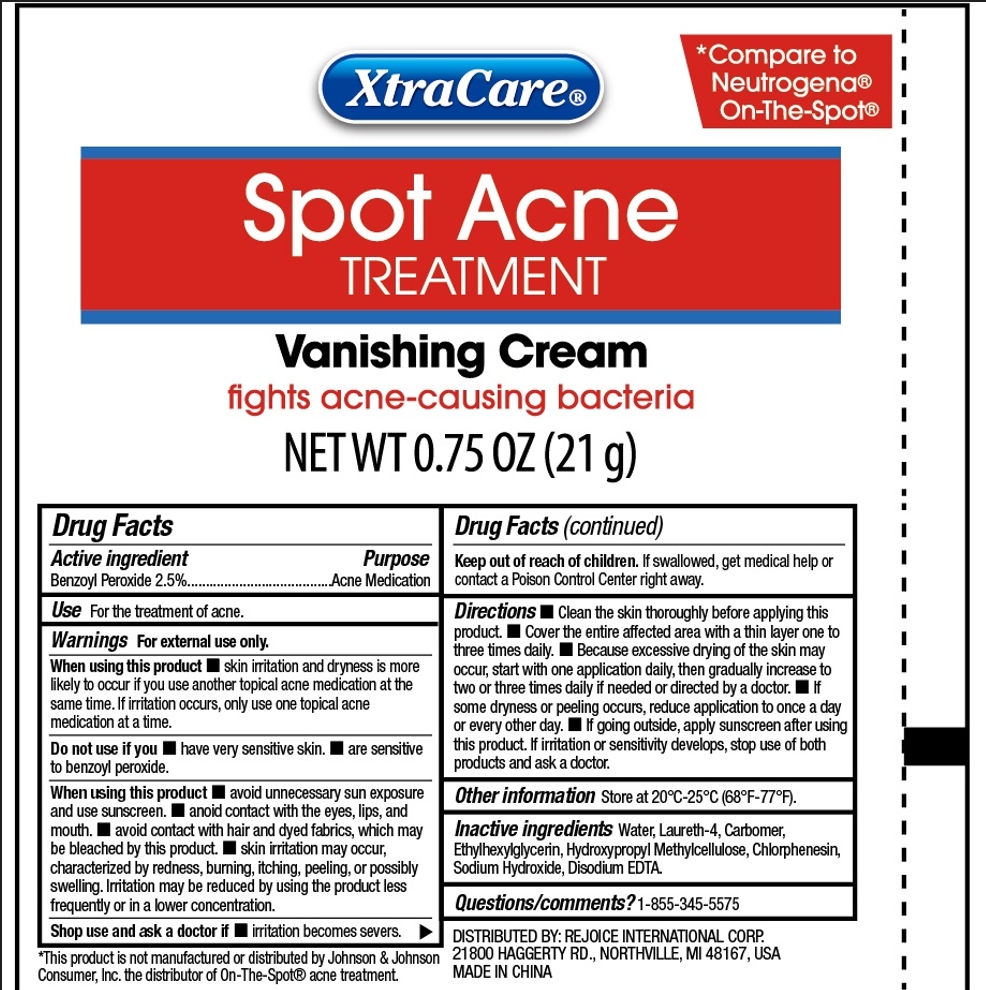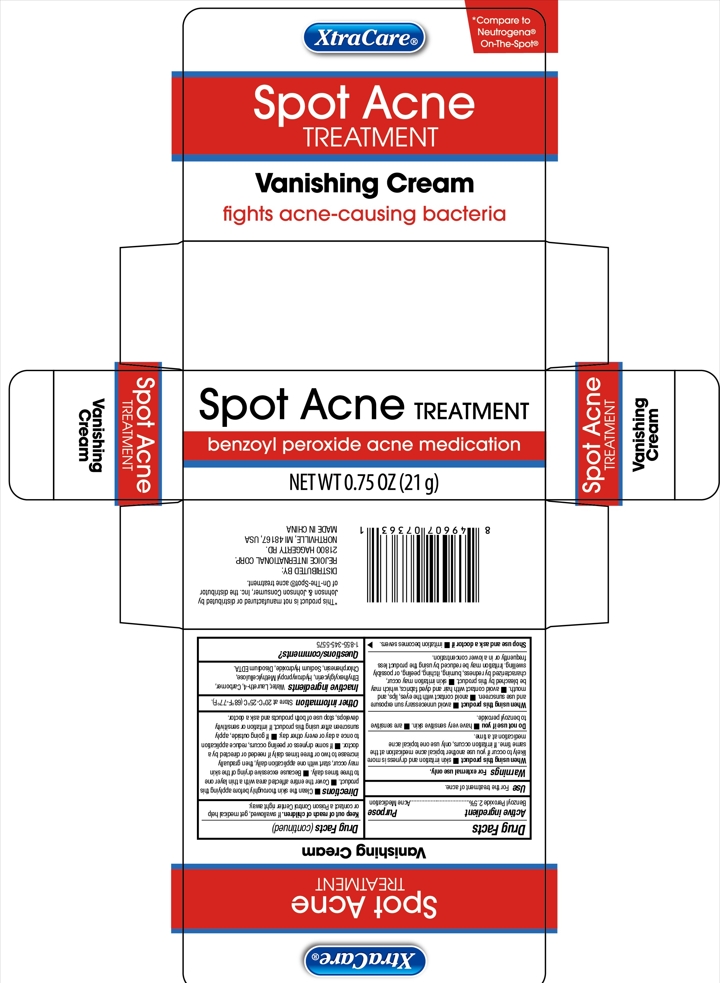 DRUG LABEL: SPOT ACNE TREATMENT 0.75OZ
NDC: 58503-168 | Form: GEL
Manufacturer: China Ningbo Shangge Cosmetics Technology Corp.
Category: otc | Type: HUMAN OTC DRUG LABEL
Date: 20231004

ACTIVE INGREDIENTS: BENZOYL PEROXIDE 2.5 g/100 g
INACTIVE INGREDIENTS: CARBOMER HOMOPOLYMER, UNSPECIFIED TYPE; ETHYLHEXYLGLYCERIN; CHLORPHENESIN; WATER; LAURETH-4; HYPROMELLOSES; SODIUM HYDROXIDE; EDETATE DISODIUM ANHYDROUS

Active ingredient

Benzoyl Peroxide 2.5%

Purpose

Acne Medication

Use

For the treatment of acne

Warnings

For external use only

When using this product

skin irritation and dryness is more likely to occur if you use another topical acne medication at the same time. If irritation occurs, only use one topical acne medication at a time.

Do not use if you

- have very sensitive skin
- are sensitive to benzoyl peroxide

When using this product

- avoid unnecessary sun exposure and use sunscreen.
- avoid contact with the eyes, lips, and mouth.
- avoid contact with hair and dyed fabrics, which may be bleached by this product.
- skin irritation may occur, charactherized by redness, burning, itching, peeling, or possibly swelling. Irritation may be reduced by using the product less frequently or in a lower concentration.

Stop use and ask a doctor if

irritation becomes severs.

Keep out of reah of children

If swallowed, get medical help or contact a Poison Control Center right away.

Directions

- Clean the skin thoroughly before applying this product.
- Cover the entire affected area with a thin layer one to three times daily.
- Because excessive drying of the skin may occur, start with one application daily, then gradually increase to two or three times daily if needed or directed by a doctor.
- if some dryness or peeling occurs, reduce application to once a day or every other day.
- If going outside, apply sunscreen after using this product. If irritation or sensitivity develops, stop use of both products and ask a doctor.

Other information

Store at 20ºC-25ºC (68ºF-77ºF)

Inactive ingredients

Water

Laureth-4

Carbomer

Ethylhexylglycerin

Hydroxypropyl Methylcellulose

Chlorphenesin

Sodium Hydroxide

Disodium EDTA